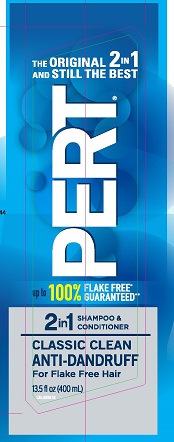 DRUG LABEL: Pert Plus 2 in 1
NDC: 41595-8001 | Form: SHAMPOO, SUSPENSION
Manufacturer: Idelle Labs, Ltd
Category: otc | Type: HUMAN OTC DRUG LABEL
Date: 20210823

ACTIVE INGREDIENTS: PYRITHIONE ZINC 1 g/100 mL
INACTIVE INGREDIENTS: WATER; AMMONIUM LAURETH-5 SULFATE; AMMONIUM LAURYL SULFATE; GLYCOL DISTEARATE; DIMETHICONE; CETYL ALCOHOL; COCO MONOETHANOLAMIDE; SODIUM CHLORIDE; GUAR HYDROXYPROPYLTRIMONIUM CHLORIDE (1.7 SUBSTITUENTS PER SACCHARIDE); HYDROGENATED POLYDECENE (550 MW); SODIUM CITRATE; SODIUM BENZOATE; POLYQUATERNIUM-10 (400 CPS AT 2%); POLYETHYLENE GLYCOL 7000; TRIMETHYLOLPROPANE TRICAPRYLATE/TRICAPRATE; CITRIC ACID MONOHYDRATE; BENZYL ALCOHOL; METHYLCHLOROISOTHIAZOLINONE; METHYLISOTHIAZOLINONE; FD&C BLUE NO. 1; D&C YELLOW NO. 10

Pert Plus 2 in 1 Shampoo and Conditioner Anti-Dandruff

THE ORIGINAL 2 IN ONE AND STILL THE BEST

PERT

CLASSIC CLEAN ANTI-DANDRUFF

for flake free hair*

Drug Facts

Active Ingredient

Pyrithione Zinc 1%

Purpose

Antidandruff

INDICATIONS AND USAGE

Use Controls the symptoms of dandruff

Warnings

For external use only

When using this product

- avoid contact with eyes. If contact occurs, rinse eyes thoroughly with water.

Stop use and ask a doctor if

- condition worsens or does not improve after regular use of this product as directed.

Keep out of reach of children. If swallowed, get medical help or contact a Poison Control Center right away.

Directions

- For best results, use at least twice a week or as directed by a doctor.
- Shake before use.
- Gently massage into wet hair, lather and rinse. Repeat if desired.

INACTIVE INGREDIENT

Inactive ingredients: Water, Ammonium Laureth Sulfate, Ammonium Lauryl Sulfate, Sodium Chloride, Glycol Distearate, Dimethicone, Fragrance, Polyquaternium 10, Guar Hydroxypropyltrimonium Chloride, Cocamide MEA, Cetyl Alcohol, PEG-7M, Trimethylolpropane tricaprylate/tricaprate, Hydrogenated Polydecene, Sodium Benzoate, Citric Acid, Sodium Citrate, Benzyl Alcohol, Methylchloroisothiazolinone, Methylisothiazolinone, Blue 1, Yellow 10.

Questions or Comments?

1-800-487-7273 www.pert.com

*visible flakes; with regular use

© 2018 Idelle Labs, Ltd. All rights reserved

Made in Canada.

Distributed by Idelle Labs, Ltd., El Paso, TX 79912 USA.

PACKAGE LABEL

THE ORIGINAL 2 IN 1 AND STILL THE BEST

PERT®

up to 100% FLAKE FREE* GUARANTEED**

2 IN 1 SHAMPOO & CONDITIONER

CLASSIC CLEAN

ANTI-DANDRUFF

For Flake Free Hair

13.5 fl oz (400 mL)